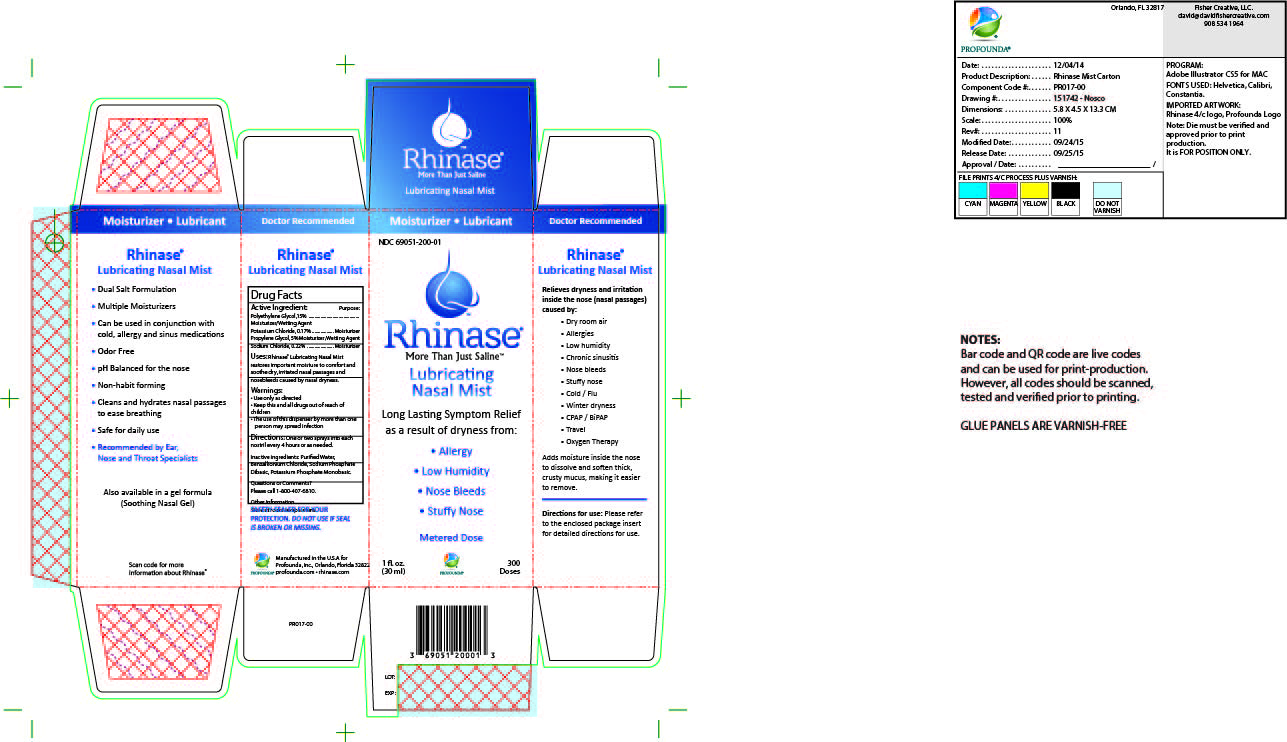 DRUG LABEL: Rhinase Lubricating Nasal Mist
NDC: 69051-200 | Form: SPRAY, METERED
Manufacturer: Profounda Inc
Category: otc | Type: HUMAN OTC DRUG LABEL
Date: 20190509

Rhinase Lubricating Nasal Mist

Inactive Ingredients

Purified water, Carbopol, Benzalkonium Chloride, Sodium Phosphate Dibasic, Potassium Phosphate monobasic

Warnings

Keep this and all drugs out of the reach of children

ACtive Ingredient

Polyethylene Glycol

Potassium Chloride

Propylene Glycol

Sodium Chloride

Directions

One or two sprays into each nostril every four hours or as needed

Indication and usage

Relieves dryness and irritation to and around the nose (nasal passages) caused by: dry room air, allergies,low humidity, chronic sinusitis, nose bleeds, stuffy nose, cold/flu, winter dryness, CPAP / BiPAP, travel, Oxygen therapy.

Adds moisture inside the nose to dissolve and soften thick, crusty mucus, making it easier to remove.

Purpose

Moisturizer / Wetting Agent

Warnings

- Use only as directed - Keep this and all drugs out of reach of children - The use of this dispensor by more than one person may spread infection